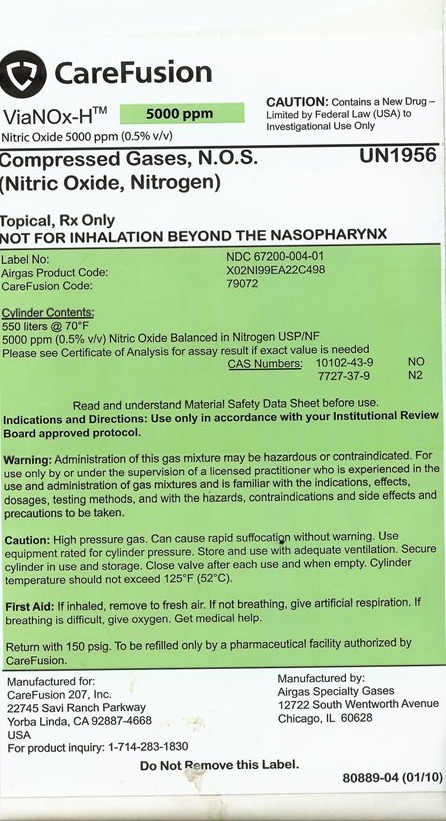 DRUG LABEL: Nitric Oxide Nitrogen Mix
NDC: 67989-011 | Form: GAS
Manufacturer: Airgas Specialty Gases
Category: prescription | Type: HUMAN PRESCRIPTION DRUG LABEL
Date: 20110311

ACTIVE INGREDIENTS: Nitric Oxide 5 mL/1 L; Nitrogen 955 mL/1 L

Nitric Oxide Nitrogen Mix

PACKAGE LABEL

CareFusion
ViaNOx-H 5000ppm Nitric Oxide 5000ppm (0.5% v/v)
CAUTION: Contains a New Drug – Limited by Federal Law (USA) to Investigational Use Only
Compressed Gases, N.O.S. (Nitric Oxide, Nitrogen) UN1956
Topical, Rx Only NOT FOR INHALATION BEYOND THE NASOPHARYNX
Label No: NDC 67200-004-01
Airgas Product Code: XO2NI99EA22C498
CareFusion Code: 79072
Cylinder Contents: 550 liters @ 70F 5000ppm (0.5% v/v) Nitric Oxide Balanced in Nitrogen USP/NF Please see Certificate of Analysis for assay result if exact value is needed
CAS Numbers: 10102-43-9 NO 7727-37-9 N2
Read and understand Material Safety Data Sheet before use. Indications and Directions: Use only in accordance with Institutional Review Board approved protocol.
WARNING: Administration of this gas mixture may be hazardous or contraindicated. For use only by or under supervision of a licensed practitioner who is experienced in the use and administration of gas mixtures and is familiar with the indications, effects, dosages, testing methods, and with the hazards, contraindications, and side effects and precautions to be taken.
CAUTION: High pressure gas. Can cause rapid suffocation without warning. Use equipment rated for cylinder pressure. Store and use with adequate ventilation. Secure cylinder in use and storage. Close valve after each use and when empty. Cylinder temperature should not exceed 125F (52C).
FIRST AID: If inhaled, remove to fresh air. If not breathing, give artificial respiration. If breathing is difficult, give oxygen. Get medical help.
Return with 150 psig. To be refilled only by a pharmaceutical facility authorized by CareFusion.
Manufactured for: CareFusion 207, Inc. 22745 Savi Ranch Parkway Yorba Linda, CA 92887-4668 USA For product inquiry: 1-314-283-1830
Manufactured by: Airgas Specialty Gases 12722 South Wentworth Avenue Chicago, IL 60628
Do Not Remove This Label. 80889-04 (01/10)